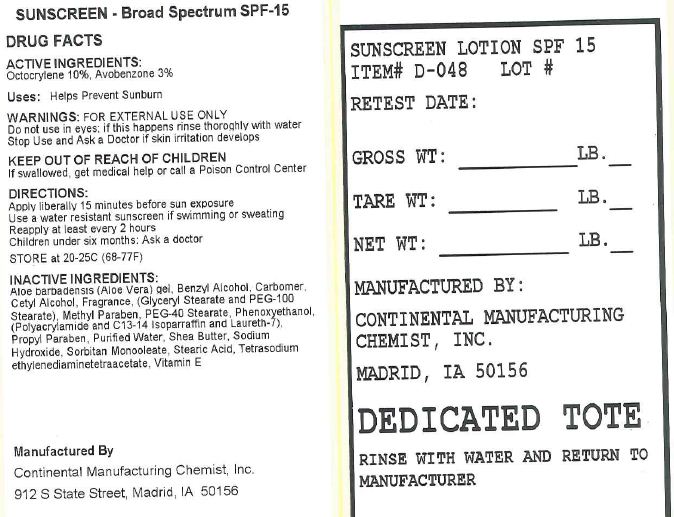 DRUG LABEL: SPF-15 Sunscreen
NDC: 49794-048 | Form: LOTION
Manufacturer: Continental Manufacturing Chemist, Inc.
Category: otc | Type: HUMAN OTC DRUG LABEL
Date: 20120708

ACTIVE INGREDIENTS: OCTOCRYLENE 100.000 g/1.0 L; AVOBENZONE 30.000 g/1.0 L
INACTIVE INGREDIENTS: ALOE VERA LEAF; BENZYL ALCOHOL; CARBOMER HOMOPOLYMER TYPE C (ALLYL PENTAERYTHRITOL CROSSLINKED); CETYL ALCOHOL; GLYCERYL MONOSTEARATE; PEG-100 STEARATE; METHYLPARABEN; PEG-40 STEARATE; PHENOXYETHANOL; SODIUM ACRYLOYLDIMETHYLTAURATE-ACRYLAMIDE COPOLYMER (1:1; 90000-150000 MPA.S); PROPYLPARABEN; WATER; SHEA BUTTER; SODIUM HYDROXIDE; SORBITAN MONOOLEATE; STEARIC ACID; EDETATE SODIUM; .ALPHA.-TOCOPHEROL

Broad-Spectrum SPF-15 Lotion

Active ingredients

Octocrylene 10%

Avobenzone 3%

Uses

Helps Prevent Sunburn

Purpose

Helps prevent sunburn

Warnings

Do not use

in eyes, if this happens rinse thoroughly with water.

Stop use and ask a doctor if

if skin irritation develops

Keep out of reach of children

If swallowed, get medical help or contact a Poison Control Center

Ask a doctor

before using on children under 6 months

Directions

Apply liberally 15 minutes before sun exposure

Use a water resistant sunscreen if swimming or sweating

Reaaply at least every 2 hours

Storage

Store at 20-25C (68-77F)

Inactive ingredients

Aloe Barbadensis (Aloe Vera) Gel, Benzyl Alcohol, Carbopol, Cetyl Alcohol, Fragrance, (Glyceryl Stearate and PEG 100 Stearate), Methyl Paraben, PEG-40 Stearate, Phenoxyethanol, (Polyacrylamide and C13-14 Isoparrafin and Laureth-7), Propyl Paraben, Purified Water, Shea Butter, Sodium Hydroxide, Sorbitan Monooleate, Stearic Acid, Tetrasodium Ethylenediaminetatraacetate, Vitamin E

Principal Display Panel

Product
SPF-15 Labels
Labels

Manufactured By

Continental Manufacturing Chemist, Inc.

912 S. State Street, Madrid, IA 50156